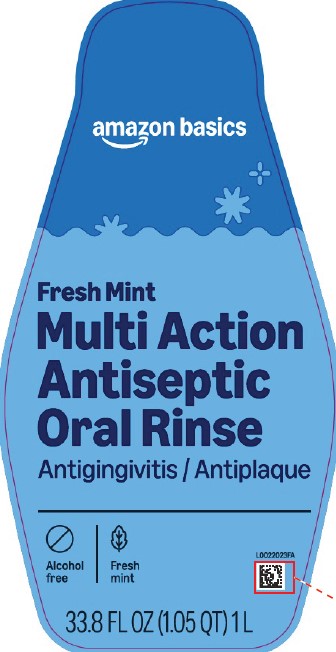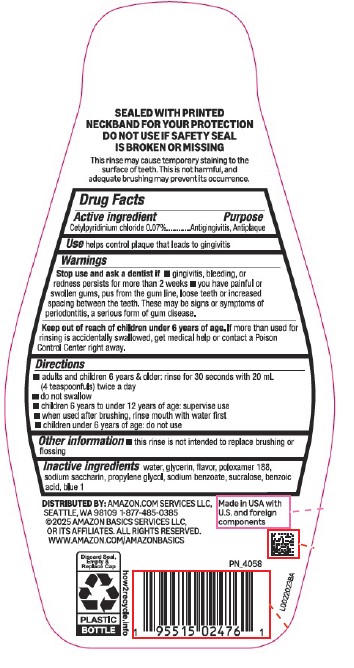 DRUG LABEL: Multi-Action Antiseptic
NDC: 72288-299 | Form: RINSE
Manufacturer: Amazon.com Services LLC
Category: otc | Type: HUMAN OTC DRUG LABEL
Date: 20250915

ACTIVE INGREDIENTS: CETYLPYRIDINIUM CHLORIDE 0.7 mg/1 mL
INACTIVE INGREDIENTS: WATER; GLYCERIN; POLOXAMER 188; SACCHARIN SODIUM; PROPYLENE GLYCOL; SODIUM BENZOATE; SUCRALOSE; BENZOIC ACID; FD&C BLUE NO. 1

Basics 299.005/299AK-AL
Multi Action Alcohol Free Antiseptic Rinse w/CPC

Tamper Evident Statement

SEALED WITH PRINTED NECKBAND FOR YOUR PROTECTION DO NOT USE IF SAFETY SEAL IS BROKEN OR MISSING.

Claims

This rinse may cause temporary staining to the surface of teeth.

This is not harmful, and adequate brushing may prevent its occurence.

active ingredient

Cetylpyridinium Chloride 0.07%

Purpose

Antigingivitis, Antiplaque

Use

helps control plaque that leads to gingivitis

Warnings

for this product

Stop use and ask a dentist if

- gingivitis, bleeding or redness persists for more than 2 weeks
- you have painful or swollen gums, pus from the gum line, loose teeth or increased spacing between the teeth. These may be signs or symptoms of periodontitis, a serious form of gum disease.

Keep out of reach of children under 6 years of age.

If more than used for rinsing is accidentally swallowed, get medical help or contact a Poison Control center right away.

Directions

- adults and children 6 years & older: rinse for 30 seconds with 20 mL (4 teaspoonfuls) twice a day
- do not swallow
- children 6 years to under 12 years of age: supervise use
- when used after brushng, rinse mouth with water first
- children under 6 years of age: do not use

Other information

- this rinse is not intended to replace brushing or flossing

inactive ingredients

water, glycerin, flavor, poloxamer 188, sodium saccharin, propylene glycol, sodium benzoate, sucralose, benzoic acid, blue 1

Adverse reactions

DISTRIBUTED BY:

Amazon.com Services LLC

Seattle, WA 98109 1-877-485-0385

©2025 Amazon Basics Services LLC or its Affiliates. All rights reserved.

www.amazon.com/amazonbasics

Made in USA with U.S. and foreign components.

Discard Seal, Empty & Replace Cap

PLASTIC BOTTLE

how2recycle.info

principal display panel

amazon basics

Fresh Mint

Multi Action

Antiseptic

Oral Rinse

Antigingivitis / Antiplaque

Alcohol Free

Fresh Mint

33.8 FL OZ (1.05 QT) 1 L